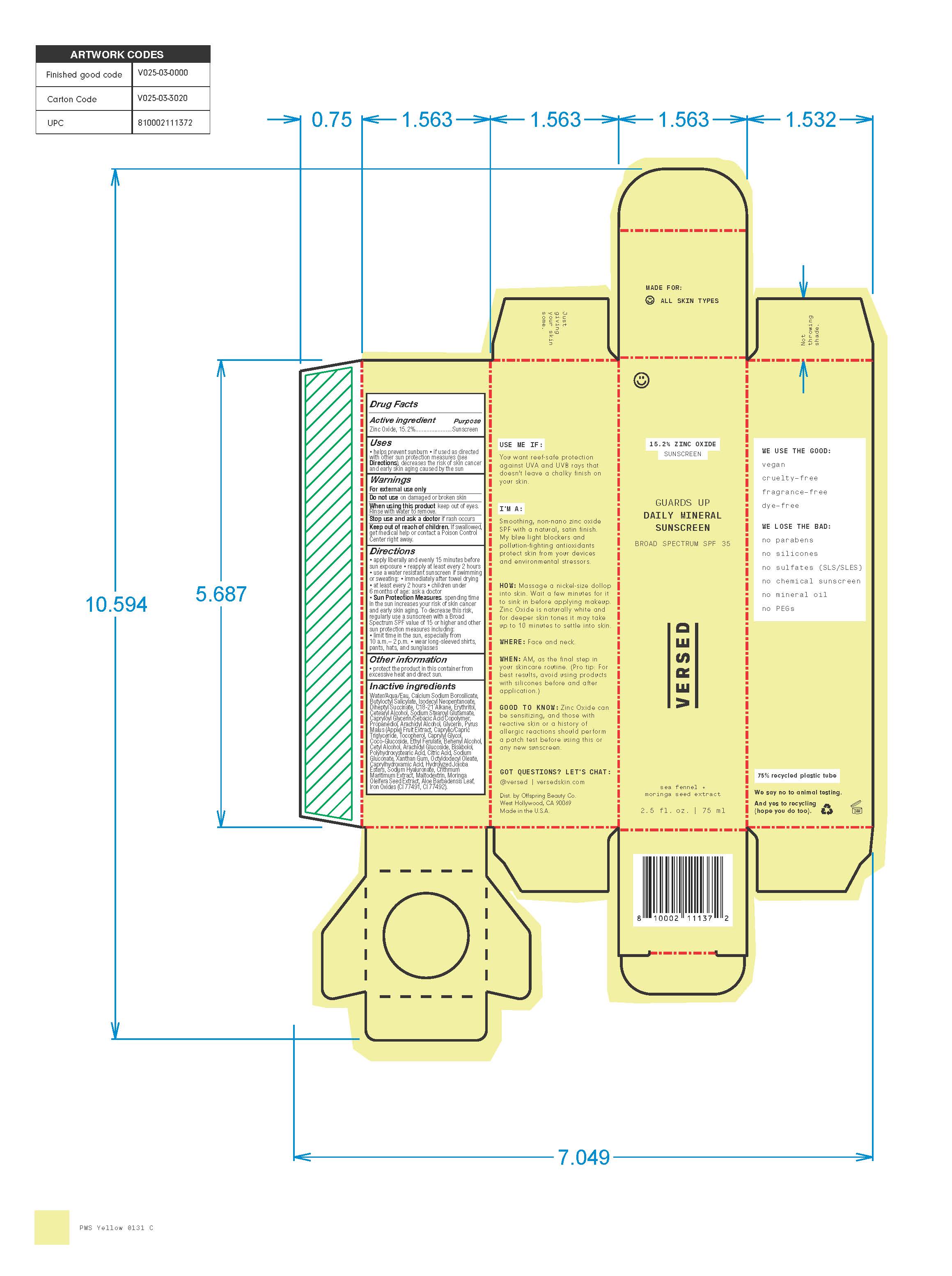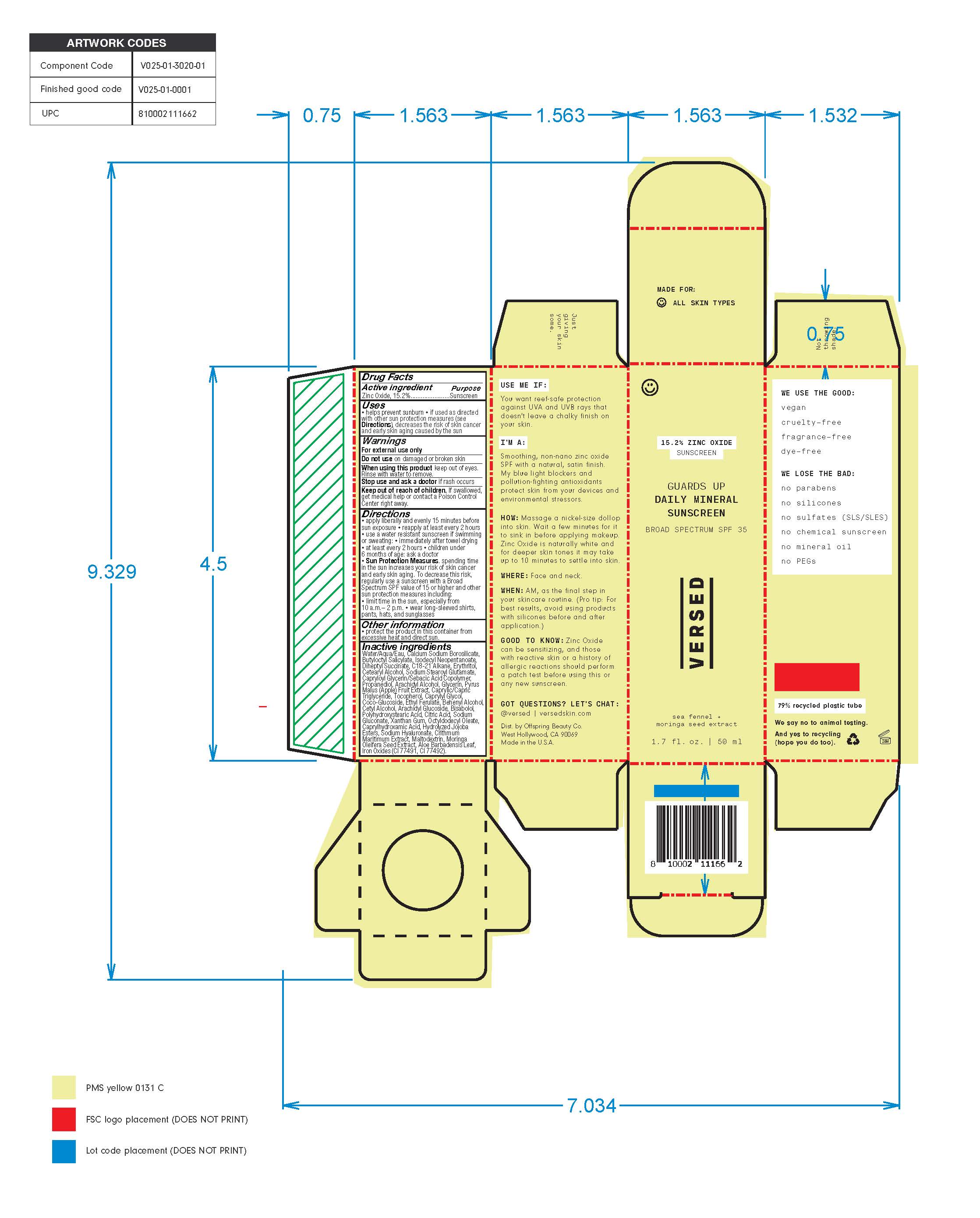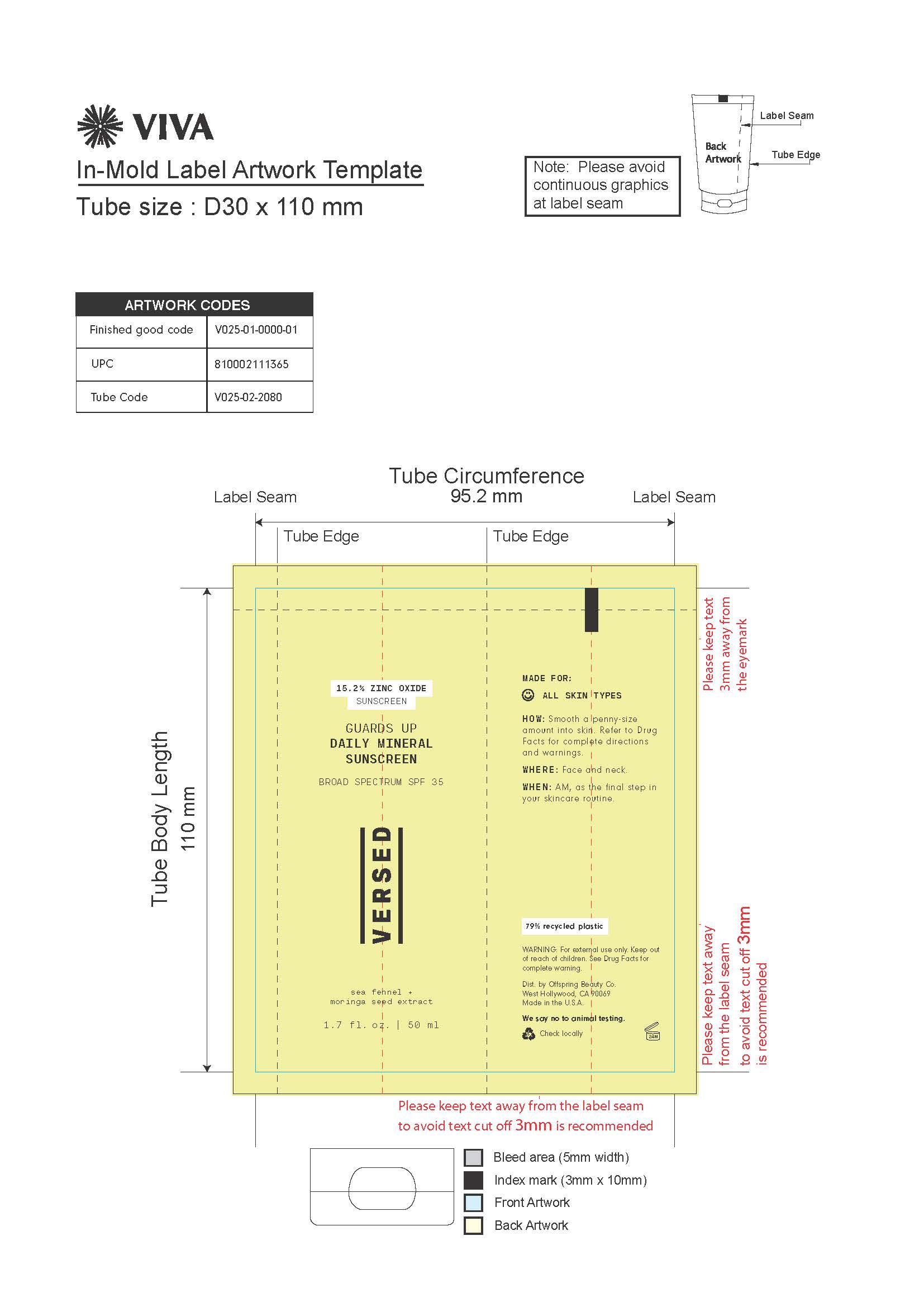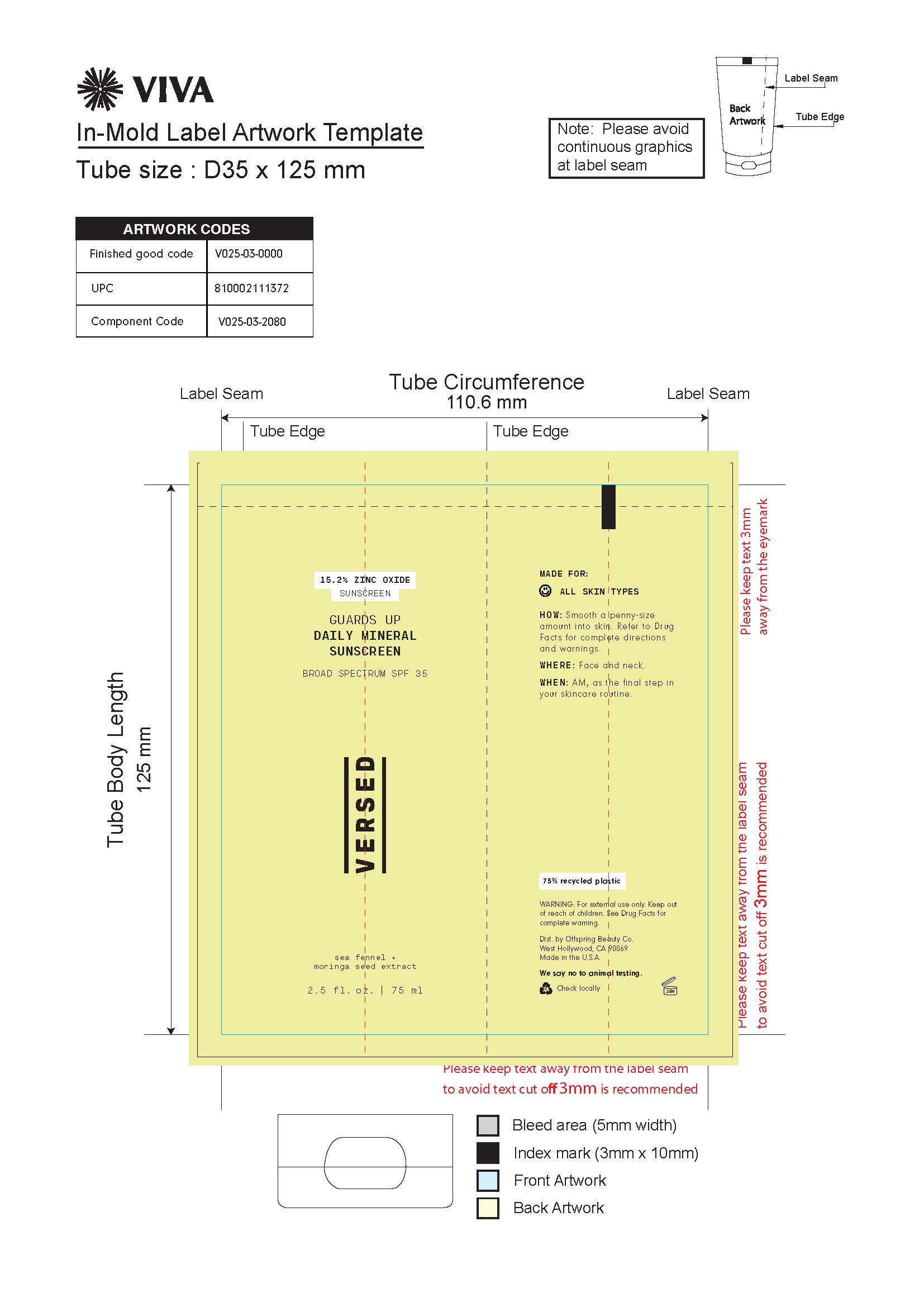 DRUG LABEL: Versed Guards Up Daily Mineral Sunscreen Broad Spectrum SPF 35
NDC: 73690-027 | Form: LOTION
Manufacturer: Offspring Beauty Co.
Category: otc | Type: HUMAN OTC DRUG LABEL
Date: 20220830

ACTIVE INGREDIENTS: ZINC OXIDE 15.2 g/100 mL
INACTIVE INGREDIENTS: C18-C21 ALKANE; ERYTHRITOL; CETOSTEARYL ALCOHOL; SODIUM STEAROYL GLUTAMATE; CITRIC ACID MONOHYDRATE; COCO GLUCOSIDE; CAPRYLHYDROXAMIC ACID; HYALURONATE SODIUM; DOCOSANOL; POLYHYDROXYSTEARIC ACID (2300 MW); CETYL ALCOHOL; PROPANEDIOL; GLYCERIN; APPLE; XANTHAN GUM; CRITHMUM MARITIMUM WHOLE; MALTODEXTRIN; ISODECYL NEOPENTANOATE; DIHEPTYL SUCCINATE; CAPRYLOYL GLYCERIN/SEBACIC ACID COPOLYMER (2000 MPA.S); FERRIC OXIDE RED; MEDIUM-CHAIN TRIGLYCERIDES; CAPRYLYL GLYCOL; LEVOMENOL; HYDROLYZED JOJOBA ESTERS (ACID FORM); SODIUM GLUCONATE; OCTYLDODECYL OLEATE; WATER; ARACHIDYL ALCOHOL; TOCOPHEROL; ETHYL FERULATE; ALOE VERA LEAF; BUTYLOCTYL SALICYLATE; FERRIC OXIDE YELLOW

Versed Guards Up Daily Mineral Sunscreen Broad Spectrum SPF 35

Active Ingredient

Zinc Oxide 15.2%

Purpose

Sunscreen

PURPOSE

Sunscreen

Uses

• Helps prevent sunburn

• If used as directed with other sun protection measures (see Directions), decreases the risk of skin cancer and early skin aging caused by the sun

Warnings

- For external use only
- Do not use on damaged or broken skin
- When using this product keep out of eyes.
- Rinse with water to remove.
- Stop use and ask a doctor if rash occurs
- Keep out of reach of children. If swallowed get medical help or contact a Poison Control Center right away.

Keep out of reach of children. If swallowed, get medical help or contact a Poison Control Center right away.

Directions

- Apply liberally and evenly 15 minutes before sun exposure
- Reapply at least every 2 hours
- Use a water resistant sunscreen if swimming or sweating, immediately after toweling drying, and at least every 2 hours
- Children under 6 months of age: ask a doctor
- Sun Protection Measures. Spending time in the sun increases your risk of skin cancer and early skin aging. To decrease this risk, regularly use a sunscreen with a Broad Spectrum SPF value of 15 or higher and othe sun protection measures including: limit time in sun, especially from 10 a.m. to 2 p.m. and wear long-sleeved shirts, pants, hats, and sunglasses

Other information

Protect this product in this container from excessive heat and direct sun.

INACTIVE INGREDIENT

Water/Aqua/Eau, Calcium Sodium Borosilicate, Butyloctyl Salicylate, Isodecyl Neopentanoate, Diheptyl Succinate, C18-21 Alkane, Erythritol, Cetearyl Alcohol, Sodium Stearoyl Glutamate, Capryloyl Glycerin/Sebacic Acid Copolymer, Propanediol, Arachidyl Alcohol, Glycerin, Pyrus Malus (Apple) Fruit Extract, Caprylic/Capric Triglyceride, Tocopherol, Caprylyl Glycol, Coco-Glucoside, Ethyl Ferulate, Behenyl Alcohol, Cetyl Alcohol, Arachidyl Glucoside, Bisabolol, Polyhydroxystearic Acid, Citric Acid, Sodium Gluconate, Xanthan Gum, Octyldodecyl Oleate, Caprylhydroxamic Acid, Hydrolyzed Jojoba Esters, Sodium Hyaluronate, Crithmum, Maritimum Extract, Maltodextrin, Moringa Oleifera Seed Extract, Aloe Barbadensis Leaf, Iron Oxides (CI 77491, CI 77492).